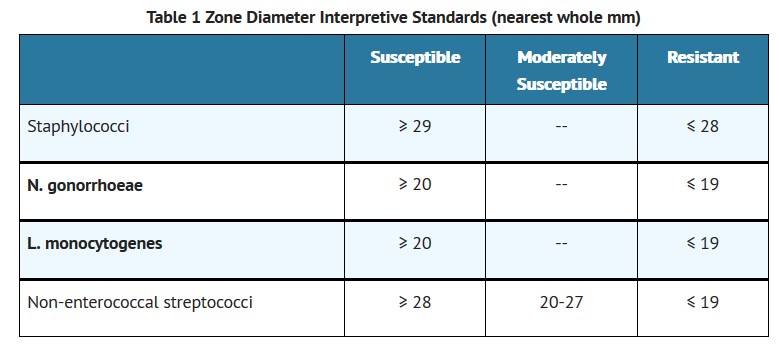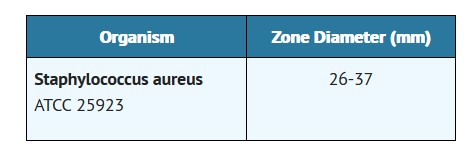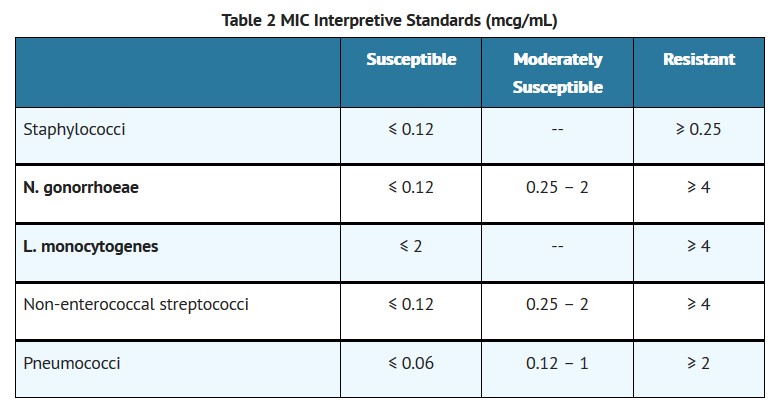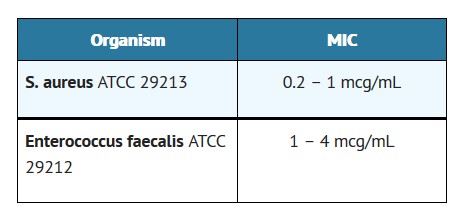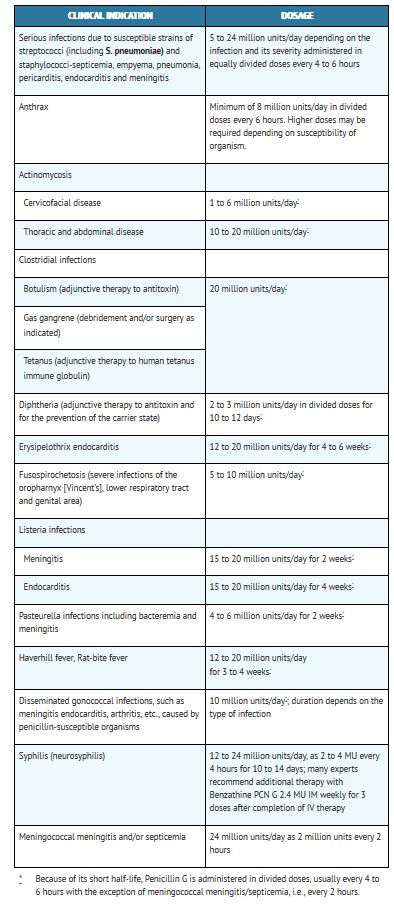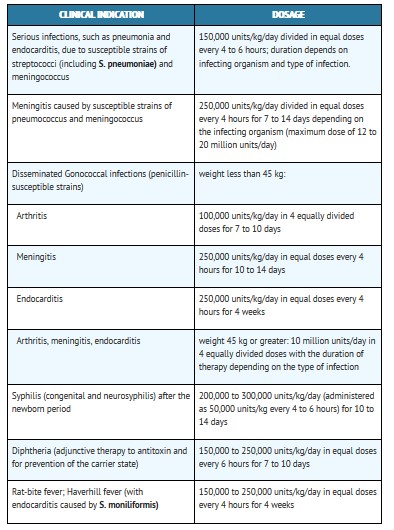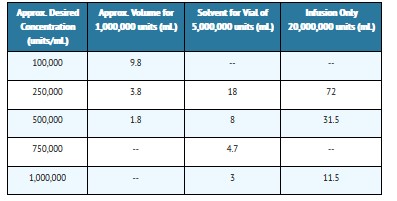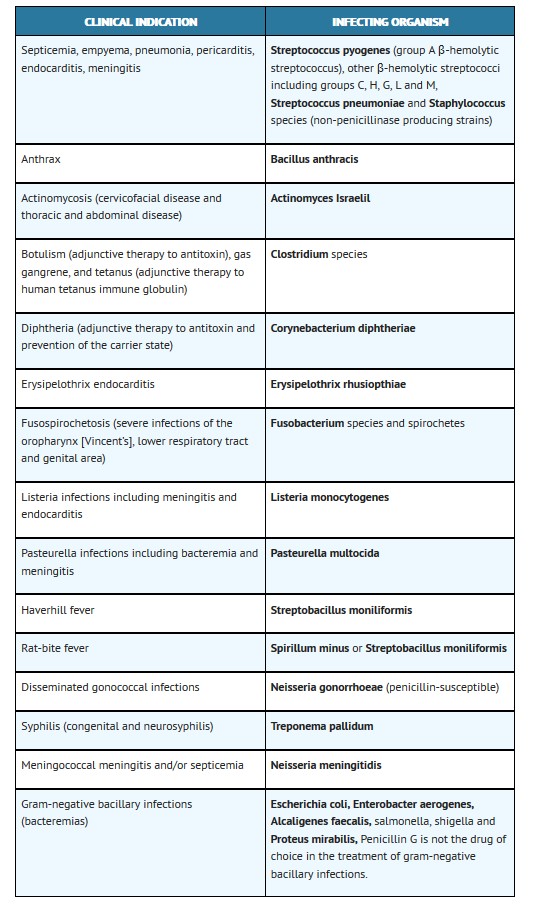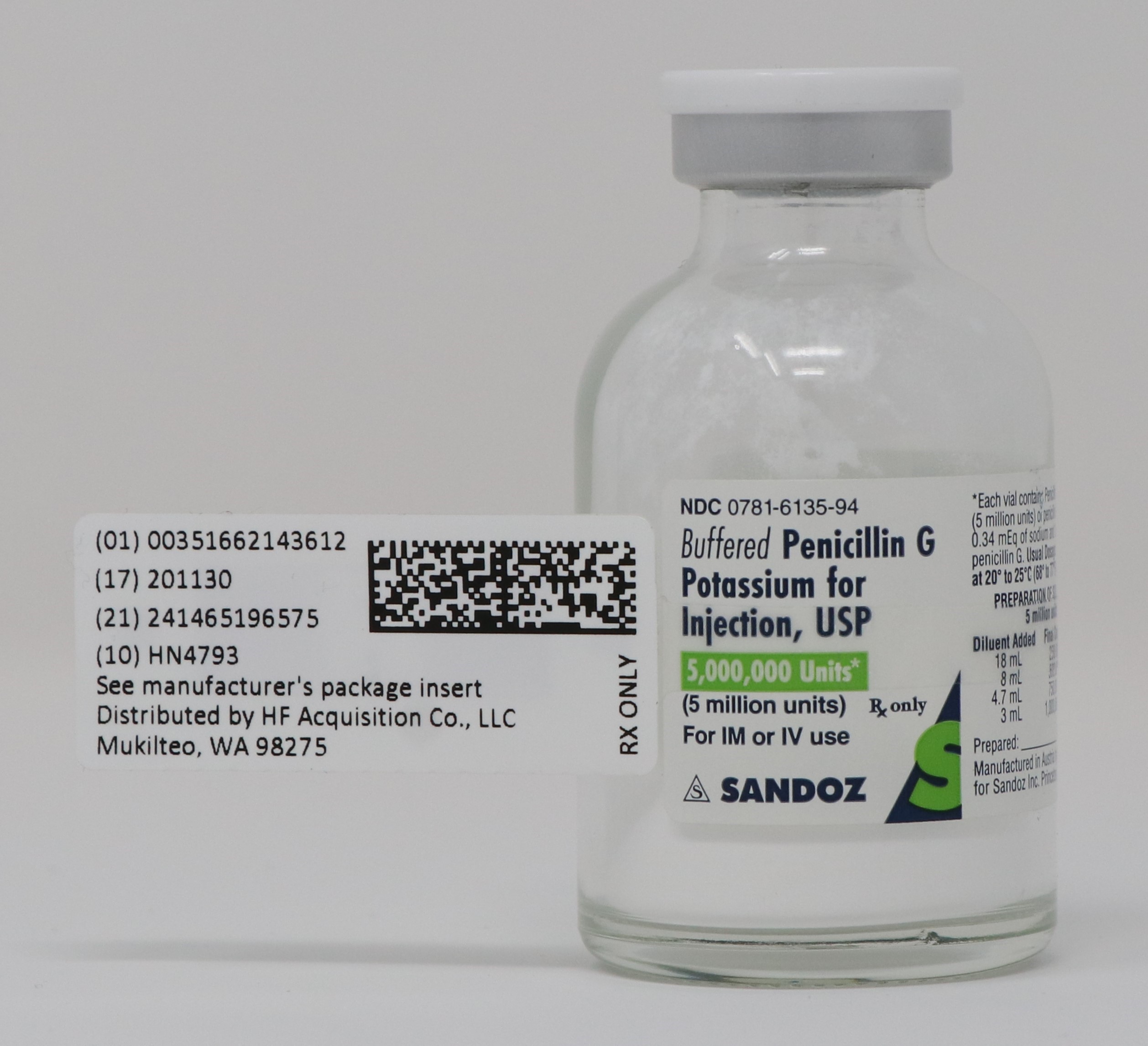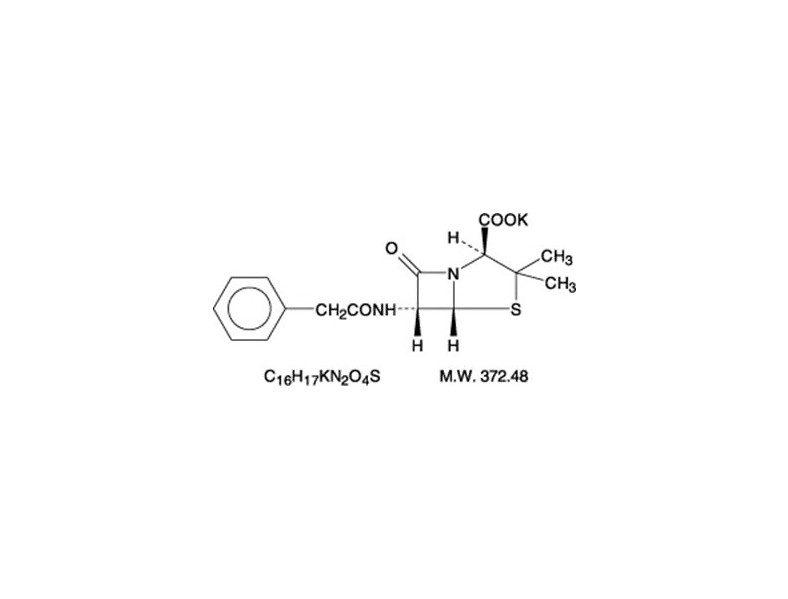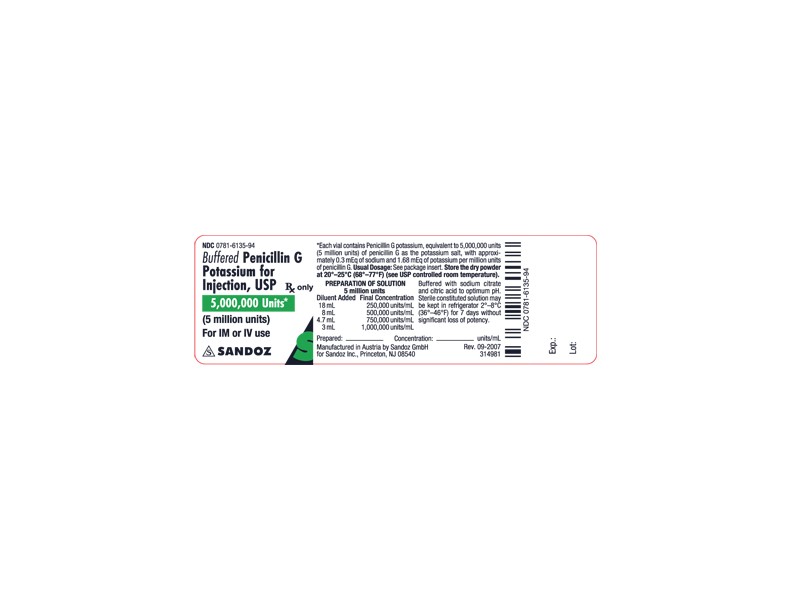 DRUG LABEL: BUFFERED PENICILLIN G POTASSIUM
NDC: 51662-1436 | Form: INJECTION, POWDER, FOR SOLUTION
Manufacturer: HF Acquisition Co LLC, DBA HealthFirst
Category: prescription | Type: HUMAN PRESCRIPTION DRUG LABEL
Date: 20250108

ACTIVE INGREDIENTS: PENICILLIN G POTASSIUM 5000000 [iU]/1 1
INACTIVE INGREDIENTS: SODIUM CITRATE, UNSPECIFIED FORM; CITRIC ACID MONOHYDRATE

BUFFERED PENICILLIN G POTASSIUM FOR INJECTION, USP 5,000,000 UNITS (5 MILLION UNITS)

SPL UNCLASSIFIED

BUFFERED

To reduce the development of drug-resistant bacteria and maintain the effectiveness of Penicillin G Potassium and other antibacterial drugs, Penicillin G Potassium should be used only to treat or prevent infections that are proven or strongly suspected to be caused by bacteria.

DESCRIPTION

Buffered Penicillin G Potassium for Injection, USP is sterile penicillin G potassium powder for reconstitution. It is an antibacterial agent intended for intravenous or intramuscularly use.

Chemically, Penicillin G Potassium is monopotassium (2S,5R,6R)-3,3-dimethyl-7-oxo-6-(2-phenylacetamido)-4-thia-1-azabicyclo (3.2.0) heptane-2-carboxylate, and has the following chemical structure:

Penicillin G potassium, a water soluble benzylpenicillin, is a white to almost white crystalline powder which is almost odorless and/or after reconstitution a colorless solution. The pH of freshly constituted solutions usually ranges from 6 to 8.5. Sodium citrate and citric acid have been added as a buffer.

Buffered Penicillin G Potassium for Injection, USP is supplied in vials equivalent to 1,000,000 units (1 million units), 5,000,000 units (5 million units), or 20,000,000 units (20 million units) of penicillin G as the potassium salt. Each million unit contains approximately 7.9 milligrams of sodium (0.34 mEq) and 65.6 milligrams of potassium (1.68 mEq).

CLINICAL PHARMACOLOGY

After an intravenous infusion of penicillin G, peak serum concentrations are attained immediately after completion of the infusion. In a study of ten patients administered a single 5 million unit dose of penicillin G intravenously over 3 to 5 minutes, the mean serum concentrations were 400 mcg/mL, 273 mcg/mL and 3 mcg/mL at 5 to 6 minutes, 10 minutes and 4 hours after completion of the injection, respectively. In a separate study, five healthy adults were administered one million units of penicillin G intravenously, either as a bolus over 4 minutes or as an infusion over 60 minutes. The mean serum concentration eight minutes after completion of the bolus was 45 mcg/mL and eight minutes after completion of the infusion was 14.4 mcg/mL.

The mean β-phase serum half-life of penicillin G administered by the intravenous route in ten patients with normal renal function was 42 minutes, with a range of 31 to 50 minutes.

The clearance of penicillin G in normal individuals is predominantly via the kidney. The renal clearance, which is extremely rapid, is the result of glomerular filtration and active tubular transport, with the latter route predominating. Urinary recovery is reported to be 58 to 85% of the administered dose. Renal clearance of penicillin is delayed in premature infants, neonates and in the elderly due to decreased renal function. The serum half-life of penicillin G correlates inversely with age and clearance of creatinine and ranges from 3.2 hours in infants 0 to 6 days of age to 1.4 hours in infants 14 days of age or older.

Nonrenal clearance includes hepatic metabolism and, to a lesser extent, biliary excretion. The latter routes become more important with renal impairment.

Probenecid blocks the renal tubular secretion of penicillin. Therefore, the concurrent administration of probenecid prolongs the elimination of penicillin G and, consequently, increases the serum concentrations.

Penicillin G is distributed to most areas of the body including lung, liver, kidney, muscle, bone and placenta. In the presence of inflammation, levels of penicillin in abscesses, middle ear, pleural, peritoneal and synovial fluids are sufficient to inhibit most susceptible bacteria. Penetration into the eye, brain, cerebrospinal fluid (CSF) or prostate is poor in the absence of inflammation. With inflamed meninges, the penetration of penicillin G into the CSF improves, such that the CSF/serum ratio is 2 to 6%. Inflammation also enhances its penetration into the pericardial fluid. Penicillin G is actively secreted into the bile resulting in levels at least 10 times those achieved simultaneously in serum. Penicillin G penetrates poorly into human polymorphonuclear leukocytes.

In the presence of impaired renal function, the β-phase serum half-life of penicillin G is prolonged. β-phase serum half-lives of one to two hours were observed in azotemic patients with serum creatinine concentrations <3 mg/100 mL and ranged as high as 20 hours in anuric patients. A linear relationship, including the lowest range of renal function, is found between the serum elimination rate constant and renal function as measured by creatinine clearance.

In patients with altered renal function, the presence of hepatic insufficiency further alters the elimination of penicillin G. In one study, the serum half-lives in two anuric patients (excreting <400 mL urine/day) were 7.2 and 10.1 hours. A totally anuric patient with terminal hepatic cirrhosis had a penicillin half-life of 30.5 hours, while another patient with anuria and liver disease had a serum half-life of 16.4 hours. The dosage of penicillin G should be reduced in patients with severe renal impairment, with additional modifications when hepatic disease accompanies the renal impairment.

Hemodialysis has been shown to reduce penicillin G serum levels.

Microbiology

Penicillin G is bactericidal against penicillin-susceptible microorganisms during the stage of active multiplication. It acts by inhibiting biosynthesis of cell-wall mucopeptide. It is not active against the penicillinase-producing bacteria, which include many strains of staphylococci. Penicillin G is highly active in vitro against staphylococci (except penicillinase-producing strains), streptococci (groups A, B, C, G, H, L and M), pneumococci and Nelsseria meningitidis. Other organisms susceptible in vitro to penicillin G are Nelsseria gonorrhoeae, Corynebacterium diphtheriae, Bacillus anthracis, clostridia, Actinomyces species, Spirillum minus, Streptobacillus monillformis, Listeria monocytogenes, and leptospira; Treponema pallidum is extremely susceptible.

Some species of gram-negative bacilli were previously considered susceptible to very high intravenous doses of penicillin G (up to 80 million units/day) including some strains of Escherichia coli, Proteus mirabilis, salmonella, shigella, Enterobacter aerogenes (formerly Aerobacter aerogenes) and Alcaligenes faecalis. Penicillin G is no longer considered a drug of choice for infections caused by these organisms.

Susceptibility Testing

Diffusion techniques

The use of antibiotic disk susceptibility test methods which measure zone diameter give an accurate estimation of antibiotic susceptibility. One such standard procedure1 which has been recommended for use with disks to test susceptibility of organisms to penicillin G uses the 10 Unit (U) penicillin disk. Interpretation involves the correlation of the diameters obtained in the disk test with the minimum inhibitory concentration (MIC) for penicillin G.

Reports from the laboratory giving results of the standard single-disk susceptibility test with a 10 U penicillin disk should be interpreted according to the following criteria:

A report of “susceptible” indicates that the pathogen is likely to be inhibited by generally achievable blood levels. A report of “moderately susceptible” suggests that the organism would be susceptible if high dosage is used or if the infection is confined to tissue and fluids (e.g., urine) in which high antibiotic levels are obtained. A report of “resistant” indicates that achievable concentrations are unlikely to be inhibitory and other therapy should be selected.

Standardized procedures require the use of laboratory control organisms. The 10 U penicillin G disk should give the following zone diameters:

Dilution techniques

When using a standardized dilution method2 (broth, agar, microdilution) or equivalent an organism may be considered susceptible if the minimum inhibitory concentration (MIC) values are interpreted according to the following table:

MIC test results should be interpreted according to the concentration of penicillin G that can be attained in blood (serum), tissue, and body fluids.

As with standard diffusion techniques, dilution methods require the use of laboratory control organisms. Standard penicillin G powder should provide the following MIC values:

For anaerobic bacteria the MIC of penicillin G can be determined by agar or broth dilution (including microdilution) techniques3.

INDICATIONS & USAGE

Therapy

Buffered Penicillin G Potassium for Injection, USP is indicated in the treatment of serious infections caused by susceptible strains of the designated microorganisms in the conditions listed below. Appropriate culture and susceptibility tests should be done before treatment in order to isolate and identify organisms causing infection and to determine their susceptibility to penicillin G. Therapy with Buffered Penicillin G Potassium for Injection, USP may be initiated before results of such tests are known when there is reason to believe the infection may involve any of the organisms listed below, however, once these results become available, appropriate therapy should be continued.

To reduce the development of drug-resistant bacteria and maintain the effectiveness of Penicillin G Potassium and other antibacterial drugs, Penicillin G Potassium should be used only to treat or prevent infections that are proven or strongly suspected to be caused by susceptible bacteria. When culture and susceptibility information are available, they should be considered in selecting or modifying antibacterial therapy. In the absence of such data, local epidemiology and susceptibility patterns may contribute to the empiric selection of therapy.

CONTRAINDICATIONS

A history of hypersensitivity (anaphylactic) reaction to any penicillin is a contraindication.

WARNINGS

SERIOUS AND OCCASIONALLY FATAL HYPERSENSITIVITY (ANAPHYLACTIC) REACTIONS HAVE BEEN REPORTED IN PATIENTS ON PENICILLIN THERAPY. THESE REACTIONS ARE MORE LIKELY TO OCCUR IN INDIVIDUALS WITH A HISTORY OF PENICILLIN HYPERSENSITIVITY AND/OR A HISTORY OF SENSITIVITY TO MULTIPLE ALLERGENS. THERE HAVE BEEN REPORTS OF INDIVIDUALS WITH A HISTORY OF PENICILLIN HYPERSENSITIVITY WHO HAVE EXPERIENCED SEVERE REACTIONS WHEN TREATED WITH CEPHALOSPORINS. BEFORE INITIATING THERAPY WITH PENICILLIN G, CAREFUL INQUIRY SHOULD BE MADE CONCERNING PREVIOUS HYPERSENSITIVITY REACTIONS TO PENICILLINS, CEPHALOSPORINS, OR OTHER ALLERGENS. IF AN ALLERGIC REACTION OCCURS, PENICILLIN G SHOULD BE DISCONTINUED AND APPROPRIATE THERAPY INSTITUTED. SERIOUS ANAPHYLACTIC REACTIONS REQUIRE IMMEDIATE EMERGENCY TREATMENT WITH EPINEPHRINE. OXYGEN, INTRAVENOUS STEROIDS, AND AIRWAY MANAGEMENT, INCLUDING INTUBATION, SHOULD ALSO BE ADMINISTERED AS INDICATED.

Pseudomembranous colitis has been reported with nearly all antibacterial agents, including penicillin G, and may range in severity from mild to life-threatening. Therefore, it is important to consider this diagnosis in patients who present with diarrhea subsequent to the administration of antibacterial agents.

Treatment with antibacterial agents alters the normal flora of the colon and may permit overgrowth of clostridia. Studies indicate that a toxin produced by Clostridium difficile is one primary cause of “antibiotic-associated colitis”.

After the diagnosis of pseudomembranous colitis has been established, therapeutic measures should be initiated. Mild cases of pseudomembranous colitis usually respond to drug discontinuation alone. In moderate to severe cases, consideration should be given to management with fluids and electrolytes, protein supplementation and treatment with an antibacterial drug effective against C. difficile.

PRECAUTIONS

General

Penicillin should be used with caution in individuals with histories of significant allergies and/or asthma (see WARNINGS). Whenever allergic reactions occur, penicillin should be withdrawn unless, in the opinion of the physician, the condition being treated is lifethreatening and amenable only to penicillin therapy.

Buffered Penicillin G Potassium for Injection, USP by the intravenous route in high doses (above 10 million units) should be administered slowly because of the potential adverse effects of electrolyte imbalance from the potassium content of the penicillin. Buffered Penicillin G Potassium for Injection, USP contains approximately 6.8 milligrams of sodium (0.3 mEq) and 65.6 milligrams of potassium (1.68 mEq) per million units of penicillin G.

The use of antibiotics may promote overgrowth of nonsusceptible organisms, including fungi. Indwelling intravenous catheters encourage superinfections. Should superinfection occur, appropriate measures should be taken.

When indicated, incision and drainage or other surgical procedures should be performed in conjunction with antibiotic therapy.

Prescribing Penicillin G Potassium in the absence of a proven or strongly suspected bacterial infection or a prophylactic indication is unlikely to provide benefit to the patient and increases the risk of the development of drug-resistant bacteria.

Laboratory Tests

Periodic assessment of organ system function, including frequent evaluation of electrolyte balance, hepatic, renal and hematopoietic systems, and cardiac and vascular status should be performed during prolonged therapy with high doses of intravenous penicillin G (see ADVERSE REACTIONS). If any impairment of function is suspected or known to exist, a reduction in the total dosage should be considered (see DOSAGE AND ADMINISTRATION).

In suspected staphylococcal infections, proper laboratory studies, including susceptibility tests should be performed.

All infections due to Group A beta-hemolytic streptococci should be treated for at least 10 days.

Patients being treated for gonococcal infection should have a serologic test for syphilis before receiving penicillin. All cases of penicillin treated syphilis should receive adequate follow-up including clinical and serological examinations. The recommended follow-up varies with the stage of syphilis being treated. See CDC recommendations.4

Drug Interactions

Bacteriostatic antibacterials (i.e., chloramphenicol, erythromycins, sulfonamides or tetracyclines) may antagonize the bactericidal effect of penicillin, and concurrent use of these drugs should be avoided. This has been documented in vitro, however, the clinical significance of this interaction is not well-documented.

Penicillin blood levels may be prolonged by concurrent administration of probenecid which blocks the renal tubular secretion of penicillins.

Other drugs may compete with Penicillin G for renal tubular secretion and thus prolong the serum half-life of penicillin. These drugs include: aspirin, phenylbutazone, sulfonamides, indomethacin, thiazide diuretics, furosemide and ethacrynic acid.

Drug/Laboratory Test Interactions

After treatment with penicillin G, a false-positive reaction for glucose in the urine may occur with Benedict’s solution, Fehling’s solution or Clinitest® tablet, but not with the enzyme-based tests, such as Clinistix®.

Penicillin G has been associated with pseudoproteinuria by certain test methods.

Carcinogenesis, Mutagenesis, Impairment of Fertility

No long-term animal studies have been conducted with this drug.

Pregnancy

Teratogenic Effects

Pregnancy Category B

Reproduction studies performed in the mouse, rat, and rabbit have revealed no evidence of impaired fertility or harm to the fetus due to penicillin G. Human experience with the penicillins during pregnancy has not shown any positive evidence of adverse effects on the fetus. There are, however, no adequate and well controlled studies in pregnant women showing conclusively that harmful effects of these drugs on the fetus can be excluded. Because animal reproduction studies are not always predictive of human response, this drug should be used during pregnancy only if clearly needed.

Nursing Mothers

Penicillins are excreted in human milk. Caution should be exercised when penicillins are administered to a nursing woman.

Pediatric Use

Incompletely developed renal function in newborns may delay elimination of penicillin; therefore, appropriate reductions in the dosage and frequency of administration should be made in these patients. All newborns treated with penicillins should be monitored closely for clinical and laboratory evidence of toxic or adverse effects (see PRECAUTIONS).

Pediatric doses are generally determined on a weight basis and should be calculated for each patient individually. Recommended guidelines for pediatric dosages are presented in DOSAGE AND ADMINISTRATION.

The potential for toxic effects in children from chemicals that may leach from the single dose premixed intravenous preparation in plastic containers has not been evaluated.

Patients should be counseled that antibacterial drugs including Penicillin G Potassium should only be used to treat bacterial infections. They do not treat viral infections (e.g., the common cold). When Penicillin G Potassium is prescribed to treat a bacterial infection, patients should be told that although it is common to feel better early in the course of therapy, the medication should be taken exactly as directed. Skipping doses or not completing the full course of therapy may: (1) decrease the effectiveness of the immediate treatment, and (2) increase the likelihood that bacteria will develop resistance and will not be treatable by Penicillin G Potassium or other antibacterial drugs in the future.

ADVERSE REACTIONS

Body as a whole

The Jarisch-Herxheimer reaction is a systemic reaction, that may occur after the initiation of penicillin therapy in patients with syphilis or other spirochetal infections (i.e., Lyme disease and Relapsing fever). The reaction begins one to two hours after initiation of therapy and disappears within 12 to 24 hours. It is characterized by fever, chills, myalgias, headache, exacerbation of cutaneous lesions, tachycardia, hyperventiliation, vasodilation with flushing and mild hypotension. The pathogenesis of the Herxheimer reaction may be due to the release from the spirochaete of host stable pyrogen.

Hypersensitivity reactions

The reported incidence of allergic reactions to all penicillins ranges from 0.7 to 10 percent in different studies (see WARNINGS). Sensitization is usually the result of previous treatment with a penicillin, but some individuals have had immediate reactions when first treated. In such cases, it is postulated that prior exposure to penicillin may have occurred via trace amounts present in milk or vaccines.

Two types of allergic reactions to penicillin are noted clinically – Immediate and delayed.

Immediate reactions usually occur within 20 minutes of administration and range in severity from urticaria and pruritus to angloneurotic edema, laryngospasm, bronchospasm, hypotension, vascular collapse and death (see WARNINGS). Such immediate anaphylactic reactions are very rare and usually occur after parenteral therapy, but a few cases of anaphylaxis have been reported following oral therapy. Another type of immediate reaction, an accelerated reaction, may occur between 20 minutes and 48 hours after administration and may include urticaria, pruritus, fever and, occasionally, laryngeal edema.

Delayed reactions to penicillin therapy usually occur within 1 to 2 weeks after initiation of therapy. Manifestations include serum sickness-like symptoms, i.e., fever, malaise, urticaria, myalgia, arthralgia, abdominal pain and various skin rashes, ranging from maculopapular eruptions to exfoliative dermatitis.

Contact dermatitis has been observed in individuals who prepare penicillin solutions.

Gastrointestinal system

Pseudomembranous colitis has been reported with the onset occurring during or after penicillin G treatment. Nausea, vomiting, stomatitis, black or hairy tongue, and other symptoms of gastrointestinal irritation may occur, especially during oral therapy.

Hematologic system

Reactions include neutropenia, which resolves after penicillin therapy is discontinued; Coombspositive hemolytic anemia, an uncommon reaction, occurs in patients treated with intravenous penicillin G in doses greater than 10 million units/day and who have previously received large doses of the drug; and with large doses of penicillin, a bleeding diathesis, can occur secondary to platelet dysfunction.

Metabolic

Buffered Penicillin G Potassium for Injection, USP (1 million units contains 0.3 mEq of sodium and 1.68 mEq of potassium) may cause serious and even fatal electrolyte disturbances, i.e., hyperkalemia, when given intravenously in large doses.

Nervous system

Neurotoxic reactions including hyperreflexia, myoclonic twitches, seizures and coma have been reported following the administration of massive intravenous doses, and are more likely in patients with impaired renal function.

Urogenital system

Renal tubular damage and interstitial nephritis have been associated with large intravenous doses of penicillin G. Manifestations of this reaction may include fever, rash, eosinophilia, proteinuria, eosinophiluria, hematuria and a rise in serum urea nitrogen. Discontinuation of penicillin G results in resolution in the majority of patients.

Local reactions

Phlebitis and thrombophlebitis may occur with intravenous administration.

OVERDOSAGE

Dose related toxicity may arise with the use of massive doses of intravenous penicillins (40 to 100 million units per day), particularly in patients with severe renal impairment (see PRECAUTIONS). The manifestations may include agitation, confusion, asterixis, hallucinations, stupor, coma, multifocal myoclonus, seizures and encephalopathy. Hyperkalemia is also possible (see ADVERSE REACTIONS – Metabolic).

In case of overdosage, discontinue penicillin, treat symptomatically and institute supportive measures as required. If necessary, hemodialysis may be used to reduce blood levels of penicillin G, although the degree of effectiveness of this procedure is questionable.

DOSAGE & ADMINISTRTION

Buffered Penicillin G Potassium for Injection, USP may be given intravenously or intramuscularly. The usual dose recommendations are as follows:

Pediatric patients

This product should not be administered to patients requiring less than one million units per dose. (see PRECAUTIONS – Pediatric Use).

Renal Impairment

Penicillin G is relatively nontoxic, and dosage adjustments are generally required only in cases of severe renal impairment.

The recommended dosage regimens are as follows: Creatinine clearance less than 10 mL/min/1.73m2; administer a full loading dose (see recommended dosages in the tables above) followed by one-half of the loading dose every 8 to 10 hours.

Uremic patients with a creatinine clearance greater than 10 mL/min/1.73m2; administer a full loading dose (see recommended dosages in the tables above) followed by one-half of the loading dose every 4 to 5 hours.

Additional dosage modifications should be made in patients with hepatic disease and renal impairment.

For most acute infections, treatment should be continued for at least 48 to 72 hours after the patient becomes asymptomatic. Antibiotic therapy for Group A β-hemolytic streptococcal infections should be maintained for at least 10 days to reduce the risk of rheumatic fever.

Parenteral drug products should be inspected visually for particulate matter and discoloration prior to administration whenever solution and container permit.

Preparation of Solution

Solutions of penicillin should be prepared as follows: Loosen powder. Hold vial horizontally and rotate it while slowly directing the stream of diluent against the wall of the vial. Shake vial vigorously after all the diluent has been added. Depending on the route of administration, use Sterile Water for Injection, USP or Sterile Isotonic Sodium Chloride Solution for Parenteral use.

Note: Penicillins are rapidly inactivated in the presence of carbohydrate solutions at alkaline pH.

Reconstitution

The following table shows the amount of solvent required for solution of various concentrations:

When the required volume of solvent is greater than the capacity of the vial, the penicillin can be dissolved by first injecting only a portion of the solvent into the vial, then withdrawing the resultant solution and combining it with the remainder of the solvent in a larger sterile container.

Penicillin G Potassium for Injection, USP is highly water soluble. It may be dissolved in small amounts of Water for Injection, or Sterile Isotonic Sodium Chloride Solution for Parenteral Use. All solutions should be stored in a refrigerator. When refrigerated, penicillin solutions may be stored for seven days without significant loss of potency.

Buffered Penicillin G Potassium for Injection may be given intramuscularly or by continuous intravenous drip for dosages of 500,000, 1,000,000 or 5,000,000 units. It is also suitable for intrapleural, intraarticular, and other local installations.

THE 20,000,000 UNIT (20 MILLION UNIT) DOSAGE MAY BE ADMINISTERED BY INTRAVENOUS INFUSION ONLY.

(1) Intramuscular Injection: Keep total volume of injection small. The intramuscular route is the preferred route of administration. Solutions containing up to 100,000 units of penicillin per mL of diluent may be used with a minimum of discomfort. Greater concentration of penicillin G per mL is physically possible and may be employed where therapy demands. When large doses are required, it may be advisable to administer aqueous solutions of penicillin by means of continuous intravenous drip.

(2) Continuous Intravenous Drip: Determine the volume of fluid and rate of its administration required by the patient in a 24-hour period in the usual manner for fluid therapy, and add the appropriate daily dosage of penicillin to this fluid. For example, if an adult patient requires 2 liters of fluid in 24 hours and a daily dosage of 10 million units of penicillin, add 5 million units of 1 liter and adjust the rate of flow so the liter will be infused in 12 hours.

(3) Intrapleural or Other Local Infusion: If fluid is aspirated, give infusion in a volume equal to 1/4 or 1/2 the amount of fluid aspirated, otherwise, prepare as for an intramuscular injection.

(4) Intrathecal Use: The intrathecal use of penicillin in meningitis must be highly individualized. It should be employed only with full consideration of the possible irritating effects of penicillin when used by this route. The preferred route of therapy in bacterial meningitides is intravenous, supplemented by intramuscular injection.

HOW SUPPLIED

BUFFERED PENICILLIN G POTASSIUM FOR INJECTION, USP is supplied in the following dosage forms.
NDC 51662-1436-1
BUFFERED PENICILLIN G POTASSIUM FOR INJECTION, USP 5,000,000 UNITS (5 MILLION UNITS)

HF Acquisition Co LLC, DBA HealthFirst
Mukilteo, WA 98275

Also supplied in the following manufacture supplied dosage forms

Buffered Penicillin G Potassium for Injection, USP, is supplied in dry powder form in vials containing 1,000,000 units (1 million units) × 10’s (NDC 0781-6134-95), 5,000,000 units (5 million units) × 10’s (NDC 0781-6135-95), and 20,000,000 units (20 million units) × 1’s (NDC 0781-6136-94) of crystalline penicillin G as the potassium salt; buffered with sodium citrate and citric acid to an optimum pH.

STORAGE

Store the dry powder at 20° to 25°C (68° to 77°F) [see USP controlled room temperature].

Sterile constituted solution may be kept in refrigerator 2° to 8°C (36° to 46°F) for 7 days without significant loss of potency.

REFERENCES

1.National Committee for Clinical Laboratory Standards, Performance Standards for Antimicrobial Disk Susceptibility Tests – Fourth Edition. Tentative Standard NCCLS Document M2-T4, Vol. 8, No. 7, NCCLS, Villanova, PA, 1988.
2.
National Committee for Clinical Laboratory Standards, Methods for Dilution Antimicrobial Susceptibility Tests for Bacteria that Grow Aerobically – Second Edition. Tentative Standard NCCLS Document M7-T2, Vol. 8, No. 8. NCCLS, Villanova, PA, 1988.
3.
National Committee for Clinical Laboratory Standards, Methods for Antimicrobial Susceptibility Testing of Anaerobic Bacteria – Second Edition. Tentative Standard NCCLS Document M11-T2, Villanova, PA, 1988 (or current M11-A2).
4.
1989 Sexually transmitted diseases treatment guidelines. MMWR 38(S-8); 5-14, Sept. 1, 1989.

SPL UNCLASSIFIED

03-2015M

46158430

46158432

Manufactured in Austria by Sandoz GmbH

for Sandoz Inc., Princeton, NJ 08540